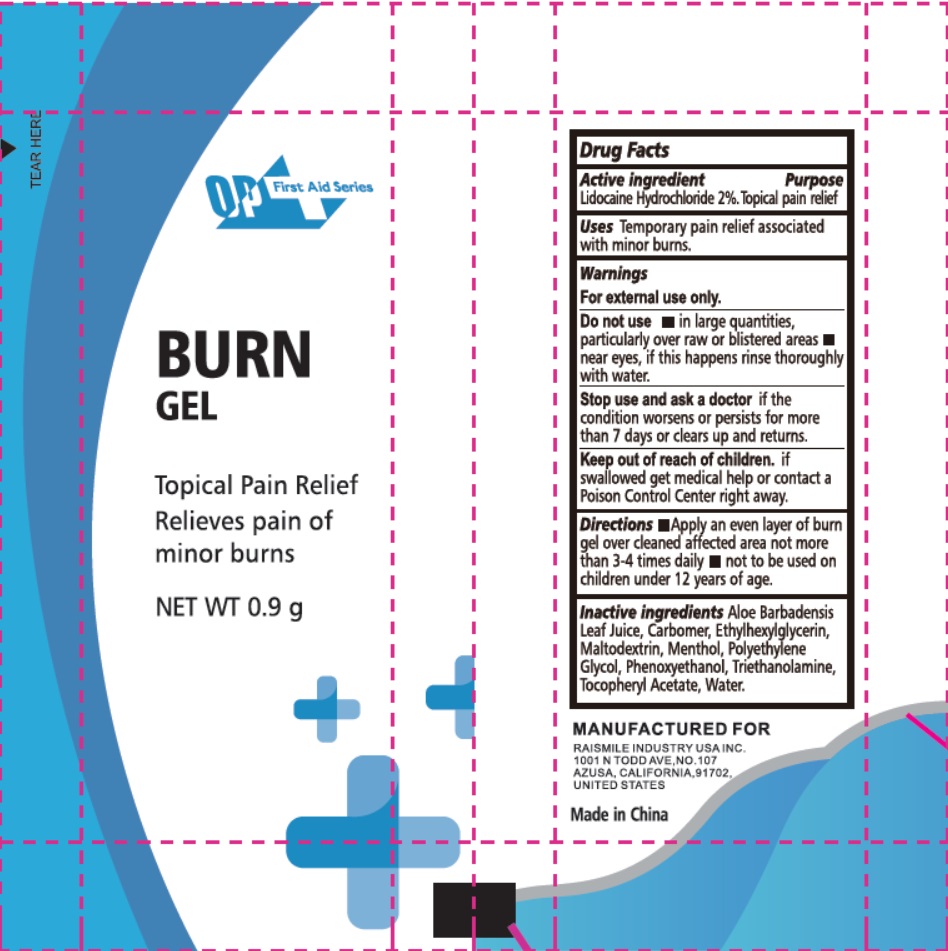 DRUG LABEL: Burn
NDC: 72459-101 | Form: GEL
Manufacturer: Yiwu Ori-Power Medtech Co., Ltd.
Category: otc | Type: HUMAN OTC DRUG LABEL
Date: 20230827

ACTIVE INGREDIENTS: LIDOCAINE HYDROCHLORIDE 20 mg/1 g
INACTIVE INGREDIENTS: ALOE VERA LEAF; CARBOMER HOMOPOLYMER, UNSPECIFIED TYPE; ETHYLHEXYLGLYCERIN; MALTODEXTRIN; MENTHOL; POLYETHYLENE GLYCOL, UNSPECIFIED; PHENOXYETHANOL; TROLAMINE; .ALPHA.-TOCOPHEROL ACETATE; WATER

Active ingredient

Lidocaine Hydrochloride 2%

Purpose

Topical pain relief

Uses

Temporary pain relief associated with minor burns.

Warnings

For external use only

Do not use

- in large quantities, particularly over raw or blistered areas.
- near eyes, if this happens rinse thoroughly with water.

Stop use and ask a doctor

if the condition worsens or persists for more than 7 days or clears up and returns.

Keep out of reach of children.

If swallowed get medical help or contact a Poison Control Center right away.

Directions

- Apply an even layer of burn gel over deaned affected area not more than 3-4 times daily
- not to be used on children under 12 years of age.

Inactive ingredients

Aloe BarbadensisLeaf Juice, Carbomer, Ethylhexgilglycerin, Maltodextrin, Menthol, Polyethylene Glycol, Phenoxyethanol, Triethanolamine, Tocopheryl Acetate, Water.